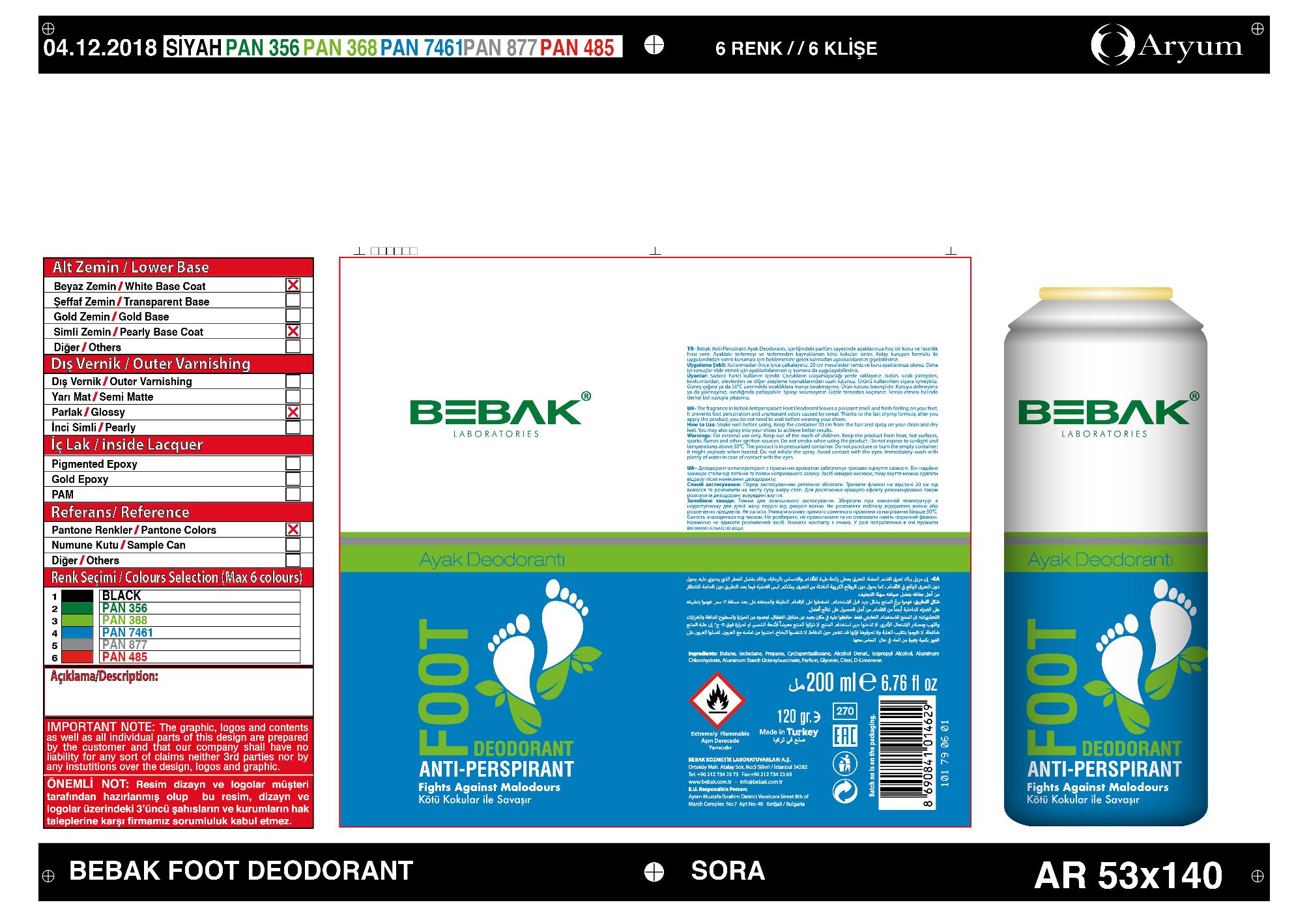 DRUG LABEL: Bebak Ayak Deodorant
NDC: 77462-007 | Form: SPRAY
Manufacturer: SORA KOZMETIK SANAYI TICARET ANONIM SIRKETI
Category: otc | Type: HUMAN OTC DRUG LABEL
Date: 20200716

ACTIVE INGREDIENTS: ALUMINUM CHLOROHYDRATE 3.78 g/200 g
INACTIVE INGREDIENTS: ALUMINUM STARCH OCTENYLSUCCINATE; GLYCERIN; CITRAL; PROPANE; BUTANE; ISOPROPYL ALCOHOL; ISOBUTANE; CYCLOMETHICONE 5; ALCOHOL; LIMONENE, (+)-

Bebak Foot Deodorant / Antiperspirant

Active Ingredient

Aluminum Chlorohydate...1.89%

Purpose

Antiperspirant

Uses

Prevent foot perspiration and odors caused by sweat.

Warnings

For External Use only.

Keep product from heat, hot surfaces, sparks, flames and their ignition sources. Do not smoke when using the product. Do not expose to sunilight and temperature above 50 degrees C. The product is in a pressurized container. Do not puncture or burn the empty container; it might explode when heated. Do not inhale spray.

WHEN USING

Avoid Contract eith eyes. Immediately wash with plenty of water in case of contact with the eyes.

Keep out of reach of children.

Directions

Keep container 20cm away and spary on your clean and dtry feet. You may also spray into your shoes to achieve better results.

Inactive Ingredients

Butane, Isobutane, Propane, Cyclopentasiloxane, Alcohol denat., Isopropyl Alcohol, Aluminum starch octenylsuccinate, parfum, glycerin, citral, d-limonene